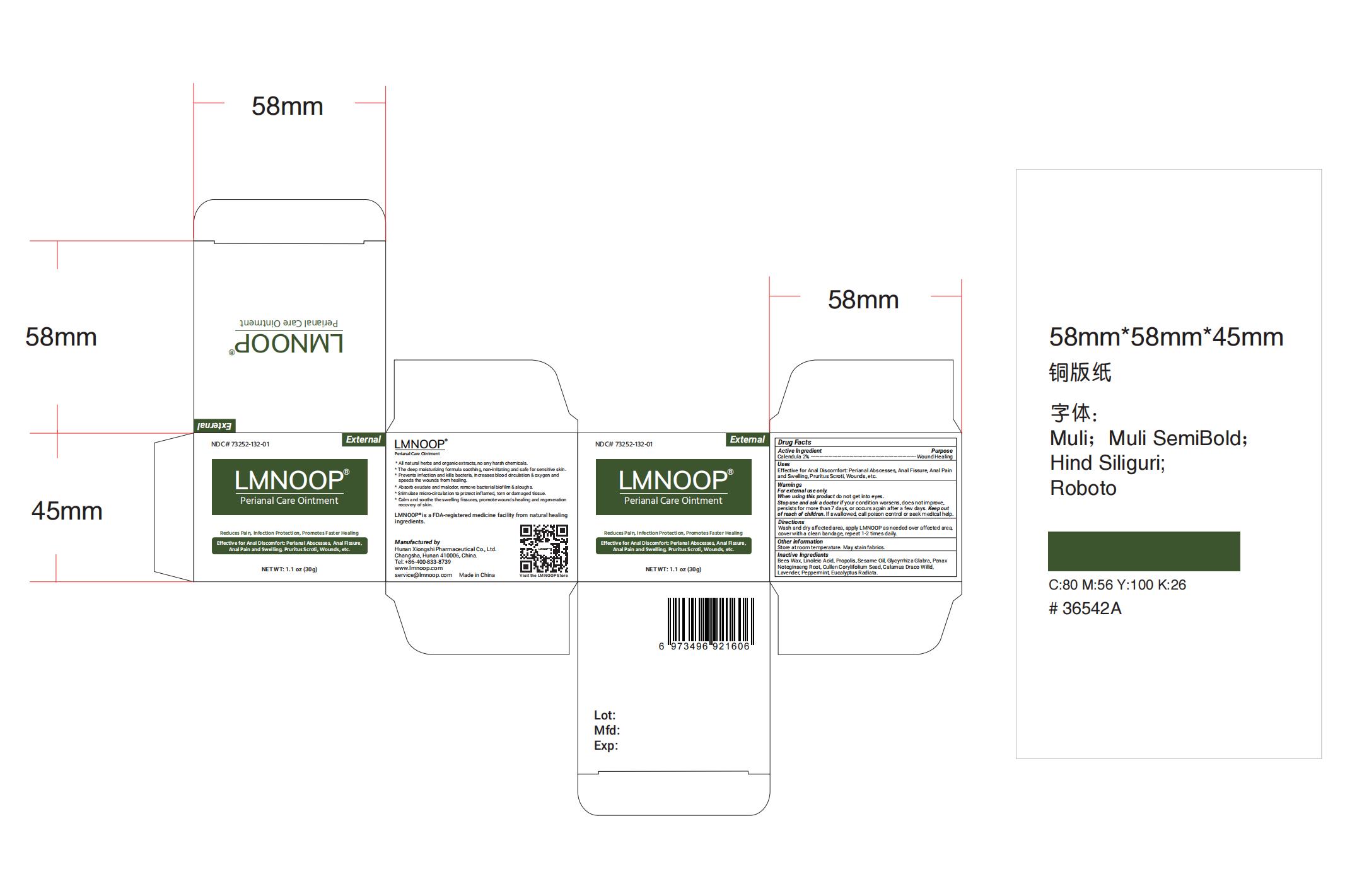 DRUG LABEL: perianal care
NDC: 73252-134 | Form: OINTMENT
Manufacturer: Hunan Xiong Shi Pharmaceutical Co., Ltd
Category: homeopathic | Type: HUMAN OTC DRUG LABEL
Date: 20241019

ACTIVE INGREDIENTS: CALENDULA OFFICINALIS FLOWER 2 g/100 g
INACTIVE INGREDIENTS: OPUNTIA ENGELMANNII WHOLE; VIOLA MANDSHURICA WHOLE; LAVENDER OIL; SESAME OIL; YELLOW WAX; PROPOLIS WAX; STYPHNOLOBIUM JAPONICUM FLOWER BUD; BORNEOL

Active lngredient

Active lngredient Purpose
Calendula 2% ----------------------------------------------------------------------- Wound Healing

Uses

Effective for Anal Discomfort: Perianal Abscesses, Anal Fissure, Anal Pain
and Swelling, Pruritus Scroti, Wounds, etc.

Directions

Wash and dry affected area, apply LMNOOP as needed over affected area,
cover with a clean bandage, repeat 1-2 times daily.

Inactive Ingredients

Bees Wax, Linoleic Acid, Propolis, Sesame Oil, Glycyrrhiza Glabra, Panax
Notoginseng Root, Cullen Corylifolium Seed, Calamus Draco Willd,
Lavender Oil.

Uses

Effective for Anal Discomfort: Perianal Abscesses, Anal Fissure, Anal Pain
and Swelling, Pruritus Scroti, Wounds, etc.

Keep out of reach of children.

Directions

Wash and dry affected area, apply LMNOOP as needed over affected area,
cover with a clean bandage, repeat 1-2 times daily.

Warnings

For external use only.
When using this product do not get into eyes.
Stop use and ask a doctor if your condition worsens, does not improve,
persists for more than 7 days, or occurs again after a few days. Keep out
of reach of children. lf swallowed, call poison control or seek medical help.